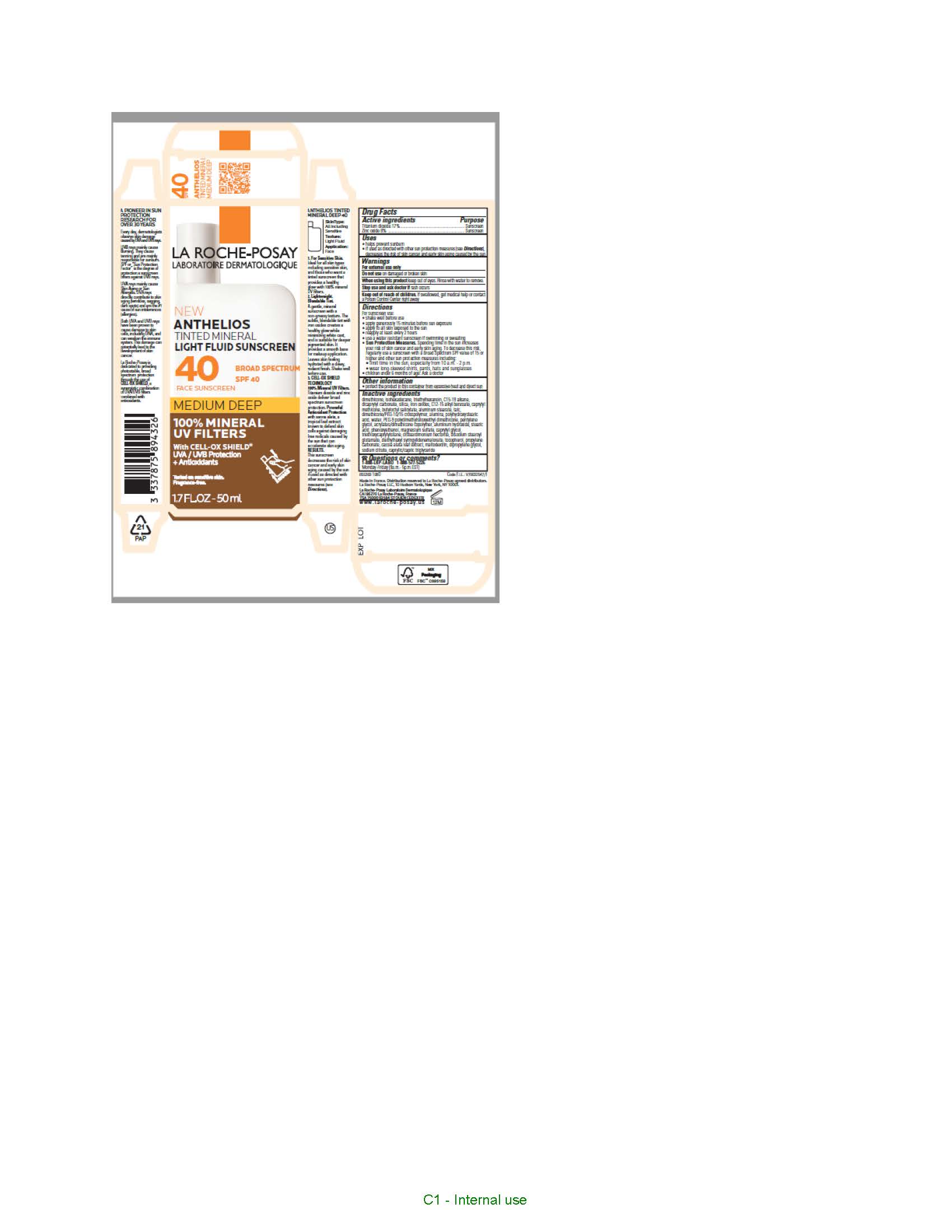 DRUG LABEL: La Roche Posay Laboratoire Dermatologique Anthelios Tinted Mineral Light Fluid Sunscreen Broad Spectrum SPF 40 Medium Deep
NDC: 49967-943 | Form: LOTION
Manufacturer: L'Oreal USA Products Inc
Category: otc | Type: HUMAN OTC DRUG LABEL
Date: 20231216

ACTIVE INGREDIENTS: Titanium dioxide 170 mg/1 mL; Zinc oxide 80 mg/1 mL
INACTIVE INGREDIENTS: ISOHEXADECANE; WATER; DIMETHICONE; TRIETHYLHEXANOIN; C15-19 ALKANE; SILICON DIOXIDE; ALKYL (C12-15) BENZOATE; CAPRYLYL TRISILOXANE; BUTYLOCTYL SALICYLATE; FERRIC OXIDE RED; ALUMINUM STEARATE; DICAPRYLYL CARBONATE; TALC; DIMETHICONE/PEG-10/15 CROSSPOLYMER; ALUMINUM OXIDE; POLYHYDROXYSTEARIC ACID (2300 MW); PEG-9 POLYDIMETHYLSILOXYETHYL DIMETHICONE; PENTYLENE GLYCOL; 2-ETHYLHEXYL ACRYLATE, METHACRYLATE, METHYL METHACRYLATE, OR BUTYL METHACRYLATE/HYDROXYPROPYL DIMETHICONE COPOLYMER (30000-300000 MW); ALUMINUM HYDROXIDE; STEARIC ACID; PHENOXYETHANOL; MAGNESIUM SULFATE, UNSPECIFIED FORM; CAPRYLYL GLYCOL; TRIETHOXYCAPRYLYLSILANE; DISTEARDIMONIUM HECTORITE; DIETHYLHEXYL SYRINGYLIDENEMALONATE; TOCOPHEROL; DISODIUM STEAROYL GLUTAMATE; PROPYLENE CARBONATE; SENNA ALATA LEAF; MALTODEXTRIN; DIPROPYLENE GLYCOL; SODIUM CITRATE; MEDIUM-CHAIN TRIGLYCERIDES

Drug Facts

Active ingredients

Titanium dioxide 17%

Zinc oxide 8%

Purpose

Sunscreen

Uses

- helps prevent sunburn
- if used as directed with other sun protection measures (see Directions), decreases the risk of skin cancer and early skin aging caused by the sun

Warnings

For external use only

Do not use

on damaged or broken skin

When using this product

keep out of eyes. Rinse with water to remove.

Stop use and ask a doctor if

rash occurs

Keep out of reach of children.

If swallowed, get medical help or contact a Poison Control Center right away.

Directions

- shake well before use
- apply generously 15 minutes before sun exposure
- apply to all skin exposed to the sun
- reapply at least every 2 hours
- use a water resistant sunscreen if swimming or sweating
- Sun Protection Measures. Spending time in the sun increases your risk of skin cancer and early skin aging. To decrease this risk, regularly use a sunscreen with a Broad Spectrum SPF value of 15 or higher and other sun protection measures including:

- limit time in the sun, especially from 10 a.m. - 2 p.m.

- wear long-sleeved shirts, pants, hats and sunglasses

- children under 6 months of age: Ask a doctor

Other information

protect the product in this container from excessive heat and direct sun

Inactive ingredients

dimethicone, isohexadecane, triethylhexanoin, c15-19 alkane, dicaprylyl carbonate, silica, iron oxides, c12-15 alkyl benzoate, caprylyl methicone, butyloctyl salicylate, aluminum stearate, talc, dimethicone/PEG-10/15 crosspolymer, alumina, polyhydroxystearic acid, water, PEG-9 polydimethylsiloxyethyl dimethicone, pentylene glycol, acrylates/dimethicone copolymer, aluminum hydroxide, stearic acid, phenoxyethanol, magnesium sulfate, caprylyl glycol, triethoxycaprylylsilane, disteardimonium hectorite, disodium stearoyl glutamate, diethylhexyl syringylidenemalonate, tocopherol, propylene carbonate, cassia alata leaf extract, maltodextrin, dipropylene glycol, sodium citrate, caprylic/capric triglyceride

Questions or comments?

1-888-LRP LABO 1-888-577-5226

Monday - Friday (9 a.m. - 5 p.m. EST)